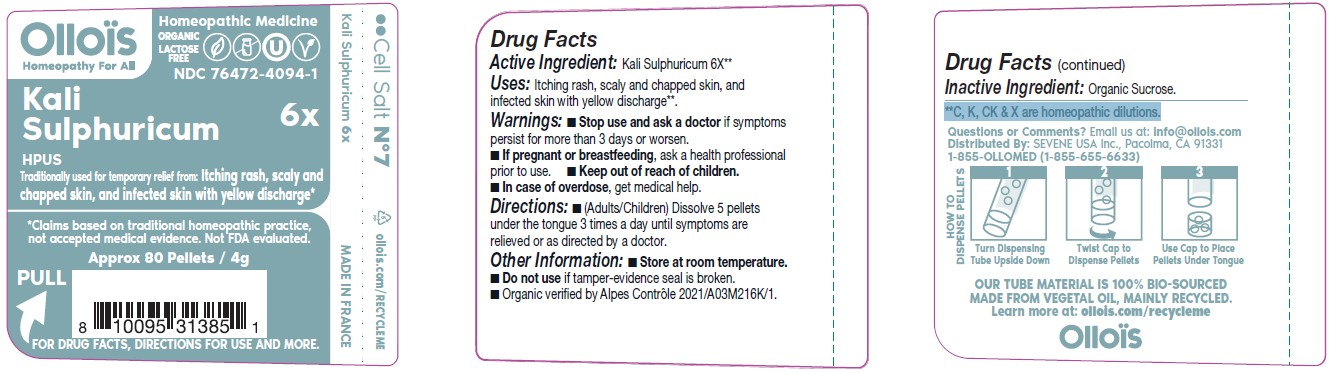 DRUG LABEL: KALI SULPHURICUM

NDC: 76472-4094 | Form: PELLET
Manufacturer: SEVENE USA
Category: homeopathic | Type: HUMAN OTC DRUG LABEL
Date: 20250211

ACTIVE INGREDIENTS: POTASSIUM SULFATE 6 [hp_X]/1 1
INACTIVE INGREDIENTS: SUCROSE

SEVENE USA (as PLD) - KALI SULPHURICUM 6X (76472-4094)

ACTIVE INGREDIENT:

KALI SULPHURICUM 6X**

**C, K, CK & X are homeopathic dilutions.

TRADITIONALLY USED FOR TEMPORARY RELIEF FROM:

Itching rash, scaly and chapped skin, and infected skin with yellow discharge*

*Claims based on traditional homeopathic practice, not accepted medical evidence. Not FDA evaluated.

DIRECTIONS:

- (adults/children) Dissolve 5 pellets under the tongue three times a day until symptoms are relieved or as directed by a doctor.

USES:

Itching rash, scaly and chapped skin, and infected skin with yellow discharge**.

**C, K, CK & X are homeopathic dilutions.

WARNINGS

- Stop use and ask a doctor if symptoms persist for more than 3 days or worsen.

PREGNANCY OR BREAST FEEDING

- If pregnant or breast-feeding, ask a health professional before use.

- Keep out of reach of children.
- In case of overdose, get medical help.

OTHER INFORMATION:

- Store at room temperature.
- Do not use if tamper-evidence seal is broken.
- Organic verified by Alpes Control 2021/A03M216K/1.

**C, K, CK & X are homeopathic dilutions

INACTIVE INGREDIENT:

ORGANIC SUCROSE

QUESTIONS OR COMMENTS?

Email us at: info@ollois.com